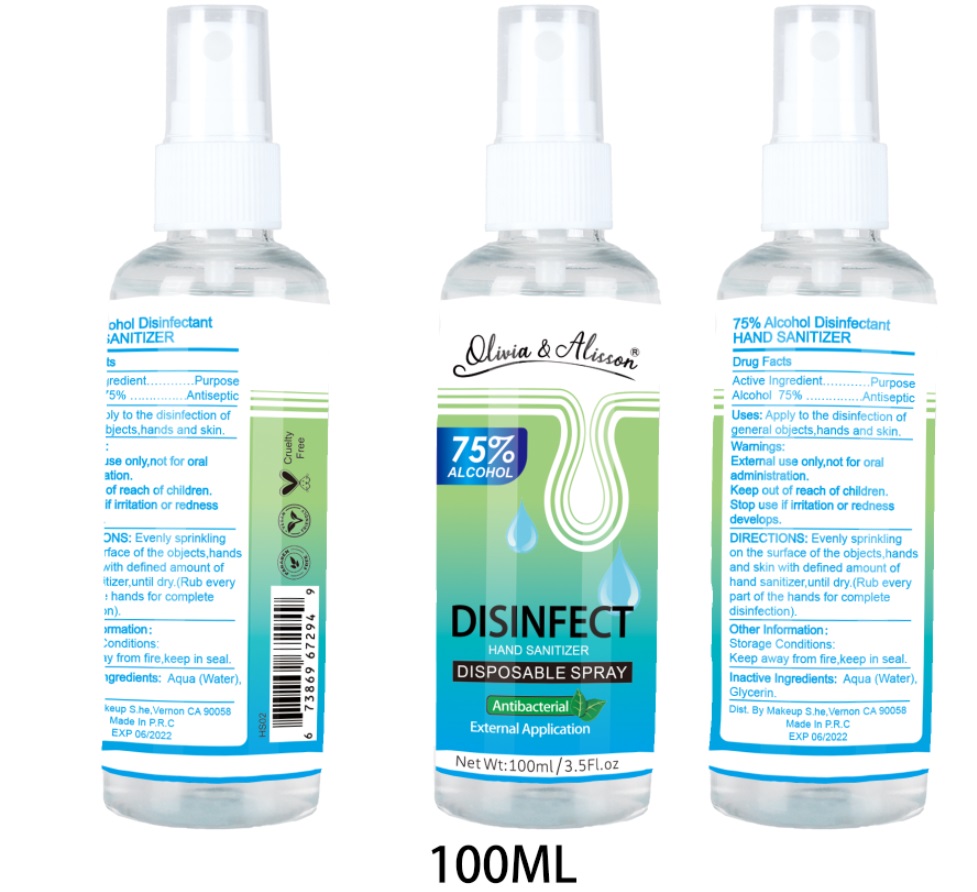 DRUG LABEL: HAND SANITIZER
NDC: 54823-006 | Form: SPRAY
Manufacturer: FUJIAN ISHINE COSMETICS CO., LTD.
Category: otc | Type: HUMAN OTC DRUG LABEL
Date: 20200506

ACTIVE INGREDIENTS: ALCOHOL 75 mL/100 mL
INACTIVE INGREDIENTS: WATER 24.5 mL/100 mL; GLYCERIN 0.5 mL/100 mL

HAND SANITIZER

Active Ingredient

ALCOHOL 75%

Purpose

Antiseptic

Uses:

Apply to the disinfection of general objects,hands and skin.

Warnings

External use only,not for oral administration.

Keep out of reach of children.

Stop use if irritation or redness develops.

Keep out of reach of children.

DIRECTIONS:

Evenly sprinkling on the surface of the objects,hands and skin with defined amount of hand sanitizer,until dry.(Rub every part of the hands for complete disinfection).

Other Information：

Storage Conditions:

Keep away from fire,keep in seal.

Inactive Ingredients:

AQUA(Water), GLYCERIN.

PACKAGE LABEL

75%ALCOHOL

DISINFECT

HAND SANITIZER

DISPOSABLE SPRAY

Antibacterial

External Application

Net Wt:100ml / 3.5fl.oz

75% Alcohol Disinfectant

HAND SANITIZER